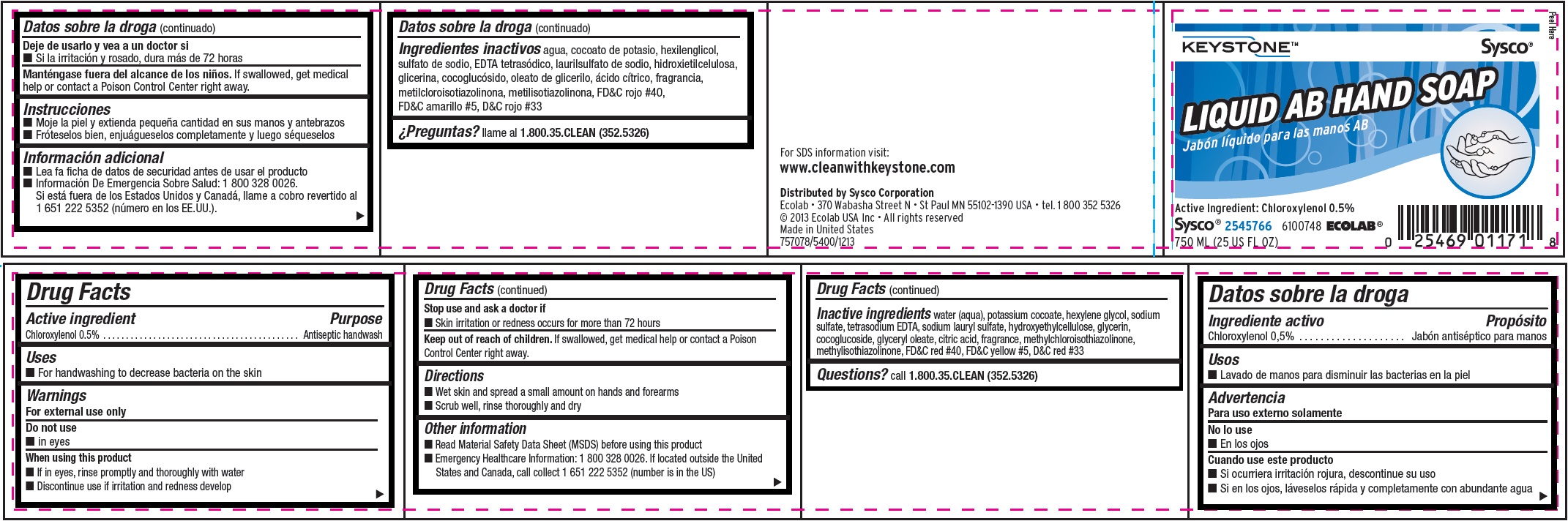 DRUG LABEL: Ecolab
NDC: 47593-465 | Form: SOLUTION
Manufacturer: Ecolab Inc.
Category: otc | Type: HUMAN OTC DRUG LABEL
Date: 20251211

ACTIVE INGREDIENTS: CHLOROXYLENOL 5 mg/1 mL
INACTIVE INGREDIENTS: WATER; POTASSIUM COCOATE; HEXYLENE GLYCOL; SODIUM SULFATE; EDETATE SODIUM; SODIUM LAURYL SULFATE; HYDROXYETHYL CELLULOSE (3000 CPS AT 1%); GLYCERIN; COCO GLUCOSIDE; GLYCERYL OLEATE; CITRIC ACID MONOHYDRATE; METHYLCHLOROISOTHIAZOLINONE; METHYLISOTHIAZOLINONE; FD&C RED NO. 40; FD&C YELLOW NO. 5; D&C RED NO. 33

Drug Facts

Active Ingredient

Chloroxylenol, 0.5%

Purpose

Antiseptic handwash

Uses

- For handwashing to decrease bacteria on the skin.

Warnings

For external use only.

Do not use

- in eyes

When using this product

- If in eyes, risne promptly and thorougly with water
- Discontinue use if irritation and redness develp

Stop use and ask a doctor if

- Skin irritation and redness occurs for more than 72 hours

Keep out of reach of children. If swallowed, get medical help, or contact a Poison Control Center right away.

Directions

- Wet skin an spread a small amount on hands and forearms
- Scrub well, rinse thoroughly and dry

Other Information

- Read Material Safety Data Sheet (MSDS) before using this product
- Emergency Healthcare Infomration : 1 800 328 0026. If located outside the United States and Canada, call collect 1 651 222 5352 (number is in the US)

INACTIVE INGREDIENT

Inactive Ingredients water (aqua), potassium cocoate, hexylene glycol, sodium sulfate, tetrasodium EDTA, sodium lauryl sulfate, hydroxyethylcellulose, glycerin, cocoglucoside, glyceryl oleate, citric acid, fragrance, methychloroisothiazolinone, methylisothiazolinone, FDC red 40, FDC yellow 5, DC red 33

Questions? call 1.800.35.CLEAN (352.5326)

Principal Display Panel and Representative Label

KEYSTONE™

Sysco®

LIQUID AB HAND SOAP

Active Ingredient: Chloroxylenol 0.5%

Sysco® 2545766

6100748 ECOLAB®

750 ML (25 US FL OZ)